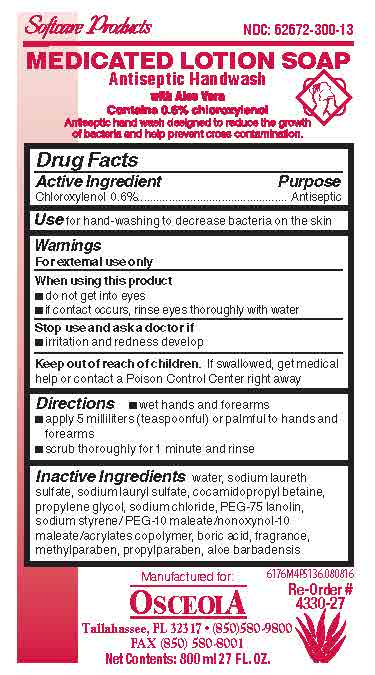 DRUG LABEL: Osceola Supply Inc 6176
NDC: 62672-300 | Form: SOAP
Manufacturer: OSCEOLA SUPPLY, INC.
Category: otc | Type: HUMAN OTC DRUG LABEL
Date: 20251119

ACTIVE INGREDIENTS: CHLOROXYLENOL 6 mg/1 mL
INACTIVE INGREDIENTS: WATER; SODIUM LAURETH SULFATE; COCAMIDOPROPYL BETAINE; PROPYLENE GLYCOL; SODIUM CHLORIDE; ALOE VERA LEAF; PROPYLPARABEN; METHYLPARABEN; BORIC ACID; SODIUM LAURYL SULFATE; PEG-75 LANOLIN

Medicated Lotion Soap 6176 Drug Facts and Label

Drug Facts Box OTC-Active Ingredient Section

Chloroxylenol 0.6%

Drug Facts Box OTC-Purpose Section

Antiseptic

Drug Facts Box OTC-Indications & Usage Section

for hand-washing to decrease bacteria on the skin

Drug Facts Box OTC-Warnings Section

For external use only

Drug Facts Box OTC-When Using Section

do not get into eyes

if contact occurs, rinse eyes thoroughly with water

Drug Facts Box OTC-Stop Use Section

irritation and redness develop

Drug Facts Box OTC-Keep Out of Reach of Children Section

if swallowed, get medical help or contact a Poison Control Center right away

Drug Facts Box OTC-Dosage & Administration Section

wet hands and forearms

apply 5 milliliters (teaspoonful) or palmful to hands and forearms

scrub thoroughly for 1 minute and rinse

Drug Facts Box OTC-Inactive Ingredient Section

water, sodium laureth sulfate, sodium lauryl sulfate, cocamidopropyl betaine, propylene glycol, sodium chloride, PEG-75 lanolin, sodium styrene/PEG-10 maleate/nonoxynol-10 maleate/acrylates copolymer, boric acid, fragrance, methylparaben, propylparaben, aloe barbadensis

Medicated Lotion Soap 6176 Label

Medicated Lotion Soap 6176 6176M4P5136.jpg